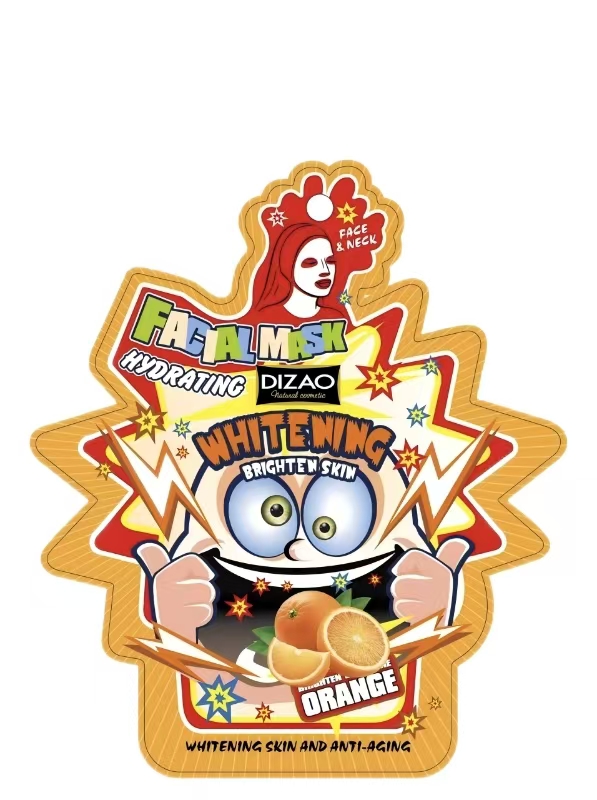 DRUG LABEL: DZ223 Orange facial mask
NDC: 84727-025 | Form: GEL
Manufacturer: Guangzhou Baishili Trading Co., Ltd
Category: otc | Type: HUMAN OTC DRUG LABEL
Date: 20241208

ACTIVE INGREDIENTS: GLYCERIN 3 g/3 mL
INACTIVE INGREDIENTS: PROPANEDIOL; WATER

PURPOSE

Contains vitamin C to help improve uneven skin tone and brighten dull skin

Warnings

For external use only.
Avoid contact with eyes. If contact occurs, rinse thoroughly with water.
Do not use on broken or irritated skin.
Stop use and ask a doctor if rash, redness, or irritation occurs.
Keep out of reach of children. If swallowed, get medical help or contact a Poison Control Center right away.

INDICATIONS AND USAGE

This product is intended for use as a skin-brightening and moisturizing facial treatment. It helps:

Improve uneven skin tone and revitalize dull skin with natural orange extract and Vitamin C.

Stop Use

Stop use and ask a doctor if:

Rash, redness, or irritation develops and persists.
You experience an allergic reaction, such as itching, swelling, or severe redness.
The product causes discomfort or excessive dryness.

Keep Out of Reach of Children

Keep out of reach of children.
If swallowed, get medical help or contact a Poison Control Center immediately.

DOSAGE AND ADMINISTRATION

For best results:

Cleanse your face thoroughly and pat dry.
Apply a generous layer of the mask evenly to the face, avoiding the eye and lip areas.
Leave on for 10–15 minutes or as directed by your healthcare provider.
Rinse off with lukewarm water and gently pat skin dry.

INACTIVE INGREDIENT

Water,Propanediol